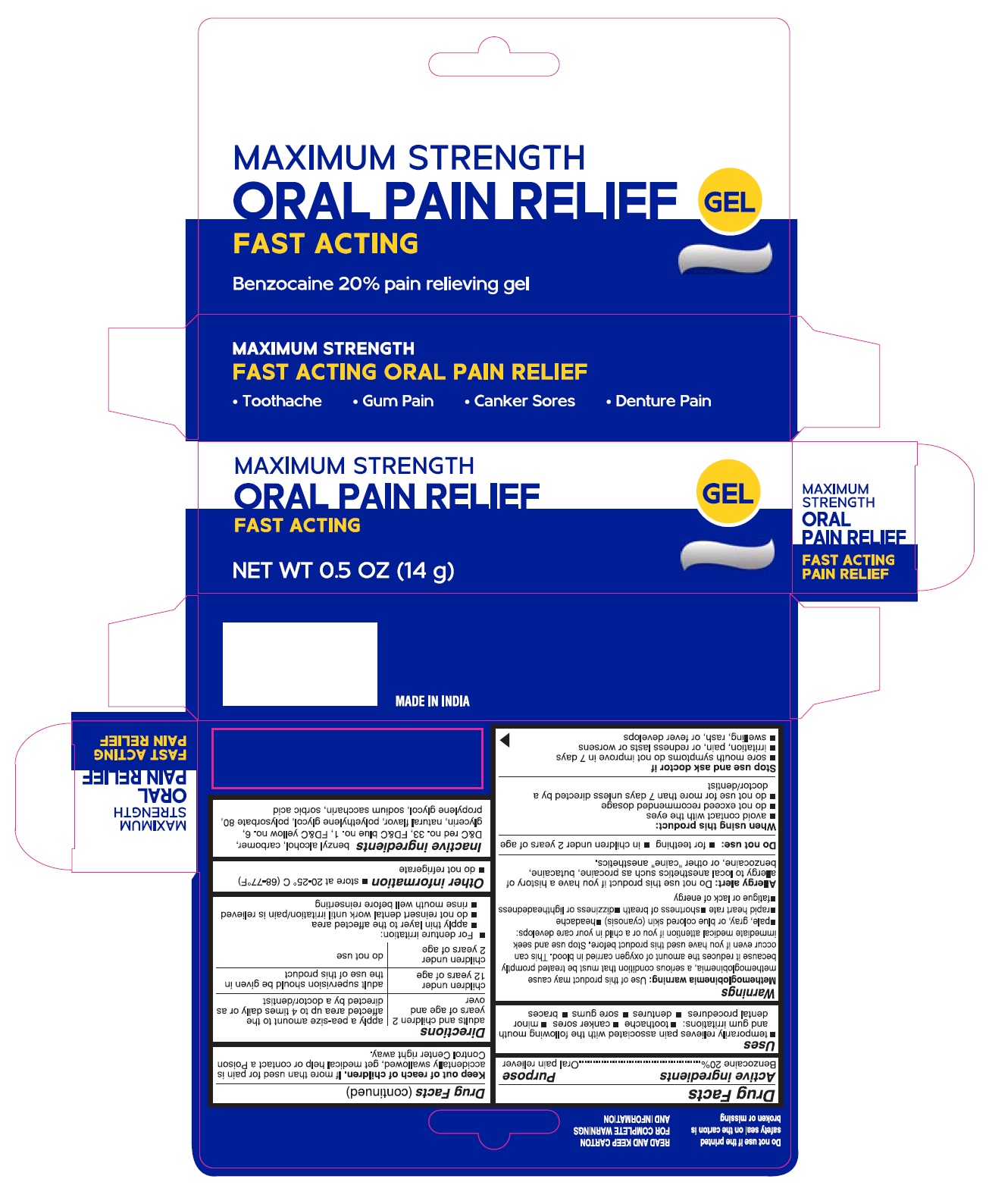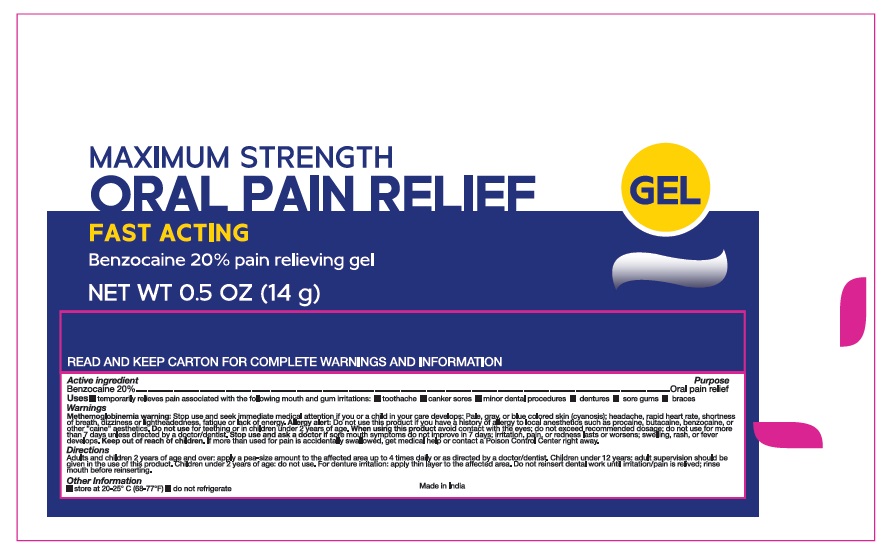 DRUG LABEL: Oral pain relief
NDC: 73492-717 | Form: GEL
Manufacturer: ALAINA HEALTHCARE PRIVATE LIMITED
Category: otc | Type: HUMAN OTC DRUG LABEL
Date: 20251209

ACTIVE INGREDIENTS: BENZOCAINE 0.2 g/1 g
INACTIVE INGREDIENTS: BENZYL ALCOHOL; CARBOMER HOMOPOLYMER, UNSPECIFIED TYPE; D&C RED NO. 33; FD&C BLUE NO. 1; FD&C YELLOW NO. 6; GLYCERIN; POLYETHYLENE GLYCOL, UNSPECIFIED; POLYSORBATE 80; PROPYLENE GLYCOL; SACCHARIN SODIUM; SORBIC ACID

MAXIMUM STRENGTH ORAL PAIN RELIEF

Drug Facts

Active ingredients Purpose

Benzocaine 20%....................................................................Oral pain reliever

Uses

- temporarily relieves pain associated with the following mouth and gum irritations:
- toothache
- canker sores
- minor dental procedures
- dentures
- sore gums
- braces

Warnings

Methemoglobinemia warning:Use of this product may cause methemoglobinemia, a serious condition that must be treated promptly because it reduces the amount of oxygen carried in blood. This can occur even if you have used this product before. Stop use and seek immediate medical attention if you or a child in your care develops:

- pale, gray, or blue colored skin (cyanosis)
- headache
- rapid heart rate
- shortness of breath
- dizziness or lightheadedness
- fatigue or lack of energy

Allergy alert:Do not use this product if you have a history of allergy to local anesthetics such as procaine, butacaine, benzocaine, or other "caine" anesthetics.

Do not use:

- for teething
- in children under 2 years of age

When using this product:

- avoid contact with the eyes
- do not exceed recommended dosage
- do not use for more than 7 days unless directed by a doctor/dentist

Stop use and ask doctor if

- sore mouth symptoms do not improve in 7 days
- irritation, pain, or redness lasts or worsens
- swelling, rash, or fever develops

Keep out of reach of children.If more than used for pain is accidentally swallowed, get medical help or contact a Poison Control Center right away.

Directions:

adults and children 2 years of age and over | apply a pea-size amount to the affected area up to 4 times daily or as directed by a doctor/dentist
children under 12 years of age | adult supervision should be given in the use of this product
children under 2 years of age | do not use

- For denture irritation:
- apply thin layer to the affected area
- do not reinsert dental work until irritation/pain is relieved
- rinse mouth well before reinserting

Other information

- store at 20-25°C (68-77°F)
- do not refrigerate

Inactive Ingredients

benzyl alcohol, carbomer, D&C red no. 33, FD&C blue no. 1, FD&C yellow no. 6, glycerin, natural flavor, polyethylene glycol, polysorbate 80, propylene glycol, sodium saccharin, sorbic acid

PACKAGE LABEL.PRINCIPAL DISPLAY PANEL

MAXIMUM STRENGTH

ORAL PAIN RELIEF GEL

FAST ACTING

Benzocaine 20% pain relieving gel

NET WT 0.5 OZ (14g)